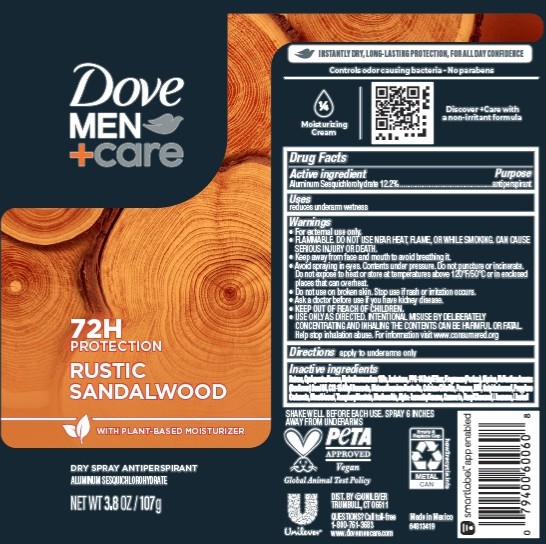 DRUG LABEL: Dove Men Care
NDC: 64942-2406 | Form: AEROSOL, SPRAY
Manufacturer: Conopco d/b/a Unilever
Category: otc | Type: HUMAN OTC DRUG LABEL
Date: 20251201

ACTIVE INGREDIENTS: ALUMINUM SESQUICHLOROHYDRATE 12.2 g/100 g
INACTIVE INGREDIENTS: HEXYL CINNAMAL; ALPHA-ISOMETHYL IONONE; NIACINAMIDE; DISTEARDIMONIUM HECTORITE; DIMETHICONOL (40 CST); BHT; HELIANTHUS ANNUUS (SUNFLOWER) SEED OIL; BUTANE; LIMONENE, (+)-; LINALOOL; GLYCINE; PROPANE; CYCLOPENTASILOXANE; HYDROFLUOROCARBON 152A; OCTYLDODECANOL; C12-15 ALKYL BENZOATE; PROPYLENE CARBONATE; COUMARIN; ISOBUTANE; PPG-14 BUTYL ETHER; CALCIUM CHLORIDE; ALPHA-TOCOPHEROL ACETATE

Dove Men + Care 72H Protection Rustic Sandalwood Dry Spray Antiperspirant

DESCRIPTION

Dove Men + Care 72H Protection Rustic Sandalwood Dry Spray Antiperspirant

ACTIVE INGREDIENT

Aluminum Sesquichlorohydrate 12.2%

PURPOSE

Antiperspirant

INDICATIONS AND USAGE

reduces underarm wetness

WARNINGS

• For external use only.
• FLAMMABLE. DO NOT USE NEAR HEAT, FLAME, OR WHILE SMOKING. CAN CAUSE SERIOUS INJURY OR DEATH.
• Keep away from face and mouth to avoid breathing it.
• Avoid spraying in eyes. Contents under pressure. Do not puncture or incinerate. Do not expose to heat or store at temperatures above 120°F/50°C or in enclosed places that can overheat.
• Do not use on broken skin. • Stop use if rash or irritation occurs.• Ask a doctor before use if you have kidney disease. • USE ONLY AS DIRECTED. INTENTIONAL MISUSE BY DELIBERATELY CONCENTRATING AND INHALING THE CONTENTS CAN BE HARMFUL OR FATAL.
Help stop inhalation abuse. For information visit www.consumered.org

• KEEP OUT OF REACH OF CHILDREN.

DOSAGE AND ADMINISTRATION

apply to underarms only

INACTIVE INGREDIENT

Butane, Cyclopentasiloxane,Hydrofluorocarbon 152a, Isobutane,PPG-14 Butyl Ether,Fragrance (Parfum),Glycine, Helianthus Annuus
(Sunflower) Seed Oil, C12-15 Alkyl Benzoate, Disteardimonium Hectorite, Calcium Chloride, Propane, BHT, Octyldodecanol, Propylene Carbonate, Dimethiconol, Tocopheryl Acetate, Niacinamide, Alpha-Isomethyl Ionone, Coumarin, Hexyl Cinnamal, Limonene, Linalool